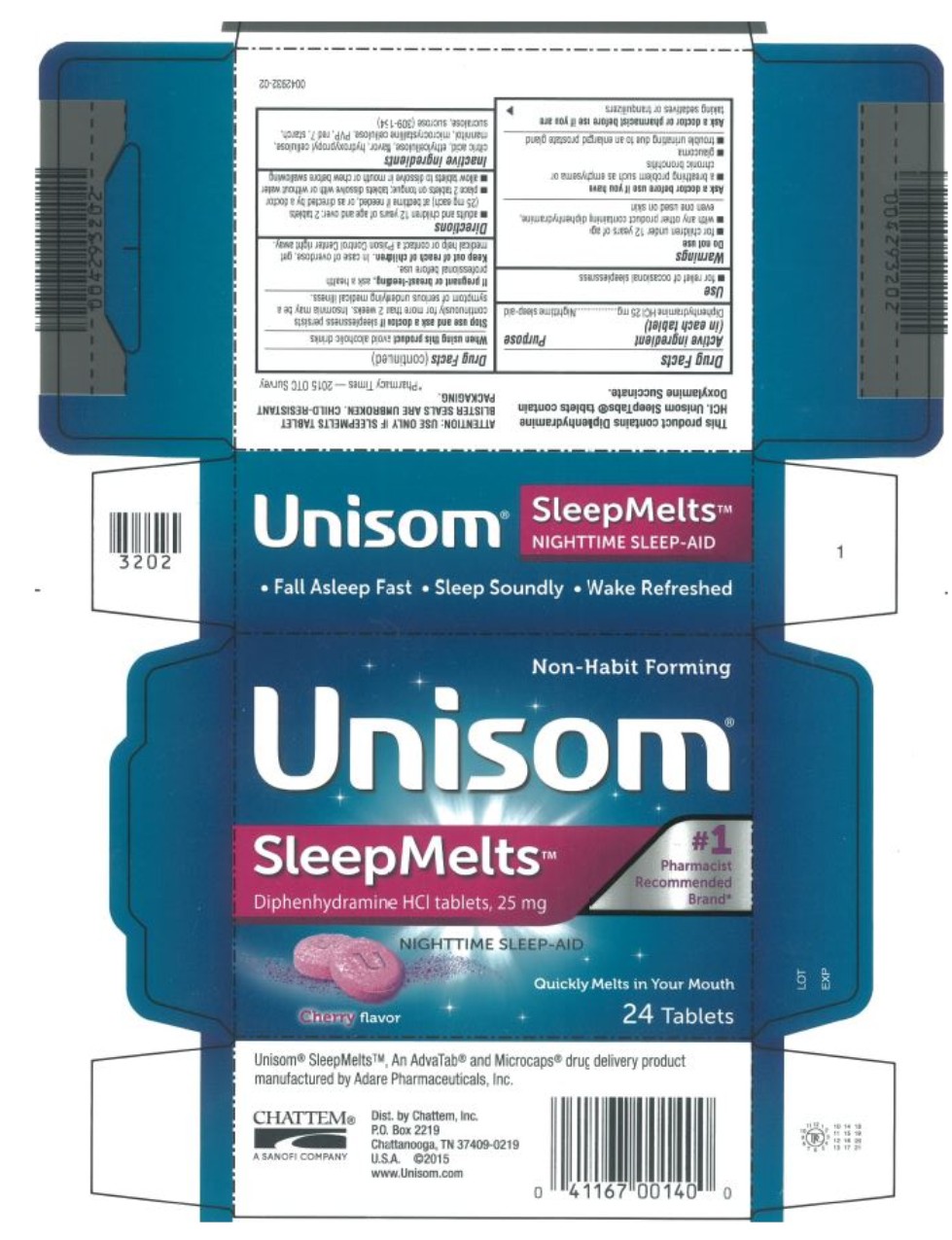 DRUG LABEL: Unisom SleepMelts Nighttime Sleep-Aid
NDC: 41167-0014 | Form: TABLET, CHEWABLE
Manufacturer: Chattem, Inc.
Category: otc | Type: HUMAN OTC DRUG LABEL
Date: 20260114

ACTIVE INGREDIENTS: DIPHENHYDRAMINE HYDROCHLORIDE 25 mg/1 1
INACTIVE INGREDIENTS: CITRIC ACID MONOHYDRATE; ETHYLCELLULOSES; HYDROXYPROPYL CELLULOSE (1600000 WAMW); MANNITOL; CELLULOSE, MICROCRYSTALLINE; POVIDONE; D&C RED NO. 7; STARCH, CORN; SUCRALOSE; SUCROSE

Unisom SleepMelts Nighttime Sleep-Aid

Drug Facts

Active ingredient

(in each caplet)

Diphenhydramine HCI 25 mg

Purpose

Nighttime sleep-aid

Uses

- for relief of occasional sleeplessness

Warnings

Do not use

- for children under 12 years of age
- with any other product containing diphenhydramine, even one used on skin

Ask a doctor before use if you have

- a breathing problem such as emphysema or chronic bronchitis
- glaucoma
- trouble urinating due to an enlarged prostate gland

Ask a doctor or pharmacist before use if you are

taking sedatives or tranquilizers

When using this product

avoid alcoholic drinks

Stop use and ask a doctor if

sleeplessness persists continuously for more than 2 weeks. Insomnia may be a symptom of serious underlying medical illness.

If pregnant or breast-feeding,

ask a health professional before use.

Keep out of reach of children.

In case of overdose, get medical help or contact a Poison Control Center right away.

Directions

- adults and children 12 years of age and over: 2 tablets (25 mg each) at bedtime if needed, or as directed by a doctor
- place 2 tablets on tongue; tablets dissolve with or without water
- allow tablets to dissolve in mouth or chew before swallowing

Inactive ingredients

citric acid, ethylcellulose, flavor, hydroxypropyl cellulose, mannitol, microcrystalline cellulose, PVP, red 7, starch, sucralose, sucrose (309-154)

Dist. by: CHATTEM, Inc.
P.O. Box 2219, Chattanooga, TN 37409 USA
© 2011 Chattem Inc. www.chattem.com

PRINCIPAL DISPLAY PANEL

Unisom®
Sleep Melts TM
Diphenhydramine HCI tablets, 25 mg
NIGHTTIME SLEEP-AID
24 Tablets